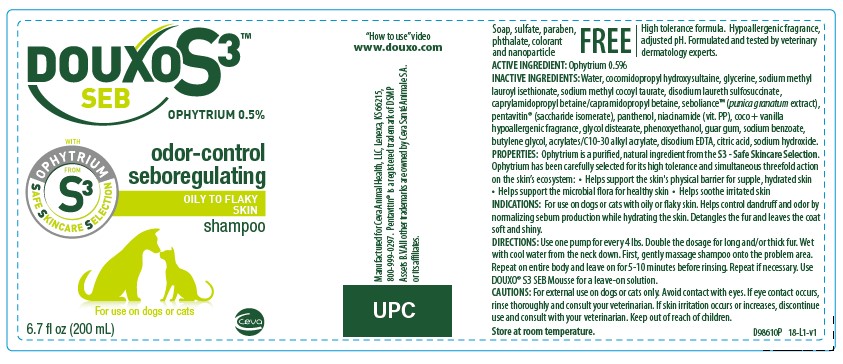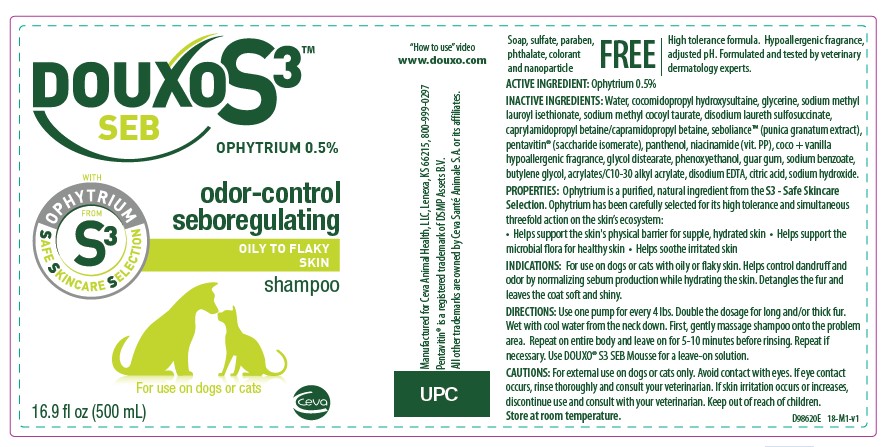 DRUG LABEL: DOUXO S3
NDC: 13744-156 | Form: SHAMPOO
Manufacturer: Ceva Sante Animale
Category: animal | Type: OTC ANIMAL DRUG LABEL
Date: 20250312

ACTIVE INGREDIENTS: OPHIOPOGON JAPONICUS ROOT 5.0 mg/1 mL
INACTIVE INGREDIENTS: COCAMIDOPROPYL HYDROXYSULTAINE; GLYCERIN; CAPRAMIDOPROPYL BETAINE; CAPRYLAMIDOPROPYL BETAINE; PUNICA GRANATUM SEED OIL; SACCHARIDE ISOMERATE; NIACINAMIDE; GLYCOL DISTEARATE; PHENOXYETHANOL; GUAR GUM; SODIUM BENZOATE; BUTYLENE GLYCOL; CARBOMER INTERPOLYMER TYPE A (ALLYL SUCROSE CROSSLINKED); EDETATE DISODIUM; CITRIC ACID MONOHYDRATE; SODIUM HYDROXIDE

DOUXO S3™ SEB

OPHYTRIUM 0.5%

Soap, sulfate, paraben, phthalate, colorant and nanoparticle FREE

High tolerance formula. Hypoallergenic fragrance, adjusted pH. Formulated and tested by veterinary dermatology experts.

ACTIVE INGREDIENT: Ophytrium 0.5%

INACTIVE INGREDIENT

INACTIVE INGREDIENTS: Water, cocomidopropyl hydroxysultaine, glycerine, sodium methyl lauroyl isethionate, sodium methyl cocoyl taurate, disodium laureth sulfosuccinate, caprylamidopropyl betaine/capramidopropyl betaine, seboliance™ (punica granatum extract),
pentavitin® (saccharide isomerate), panthenol, niacinamide (vit. PP), coco + vanilla hypoallergenic fragrance, glycol distearate, phenoxyethanol, guar gum, sodium benzoate, butylene glycol, acrylates/C10-30 alkyl acrylate, disodium EDTA, citric acid, sodium hydroxide.

DESCRIPTION

PROPERTIES: Ophytrium is a purified, natural ingredient from the S3 - Safe Skincare Selection. Ophytrium has been carefully selected for its high tolerance and simultaneous threefold action on the skin’s ecosystem:
• Helps support the skin's physical barrier for supple, hydrated skin • Helps support the microbial flora for healthy skin • Helps soothe irritated skin

INDICATIONS AND USAGE

INDICATIONS: For use on dogs or cats with oily or flaky skin. Helps control dandruff and odor by normalizing sebum production while hydrating the skin. Detangles the fur and leaves the coat soft and shiny.

DIRECTIONS: Use one pump for every 4 lbs. Double the dosage for long and/or thick fur. Wet with cool water from the neck down. First, gently massage shampoo onto the problem area. Repeat on entire body and leave on for 5-10 minutes before rinsing. Repeat if necessary. Use DOUXO® S3 SEB Mousse for a leave-on solution.

PRECAUTIONS

CAUTIONS: For external use on dogs or cats only. Avoid contact with eyes. If eye contact occurs, rinse thoroughly and consult your veterinarian. If skin irritation occurs or increases, discontinue use and consult with your veterinarian. Keep out of reach of children.

STORAGE AND HANDLING

Store at room temperature.

“How to use” video www.douxo.com

Manufactured for Ceva Animal Health, LLC, Lenexa, KS 66215, 800-999-0297
Pentavitin® is a registered trademark of DSMP Assets B.V.
All other trademarks are owned by Ceva Santé Animale S.A. or its affiliates.

PRINCIPAL DISPLAY PANEL - 200 mL Bottle

DOUXO S3™

SEB

OPHYTRIUM 0.5%

odor-control seboregulating

OILY TO FLAKY SKIN

shampoo

For use on dogs or cats

6.7 fl oz (200 mL)

PRINCIPAL DISPLAY PANEL - 500 mL Bottle

DOUXO S3™

SEB

OPHYTRIUM 0.5%

odor-control seboregulating

OILY TO FLAKY SKIN

shampoo

For use on dogs or cats

16.9 fl oz (500 mL)